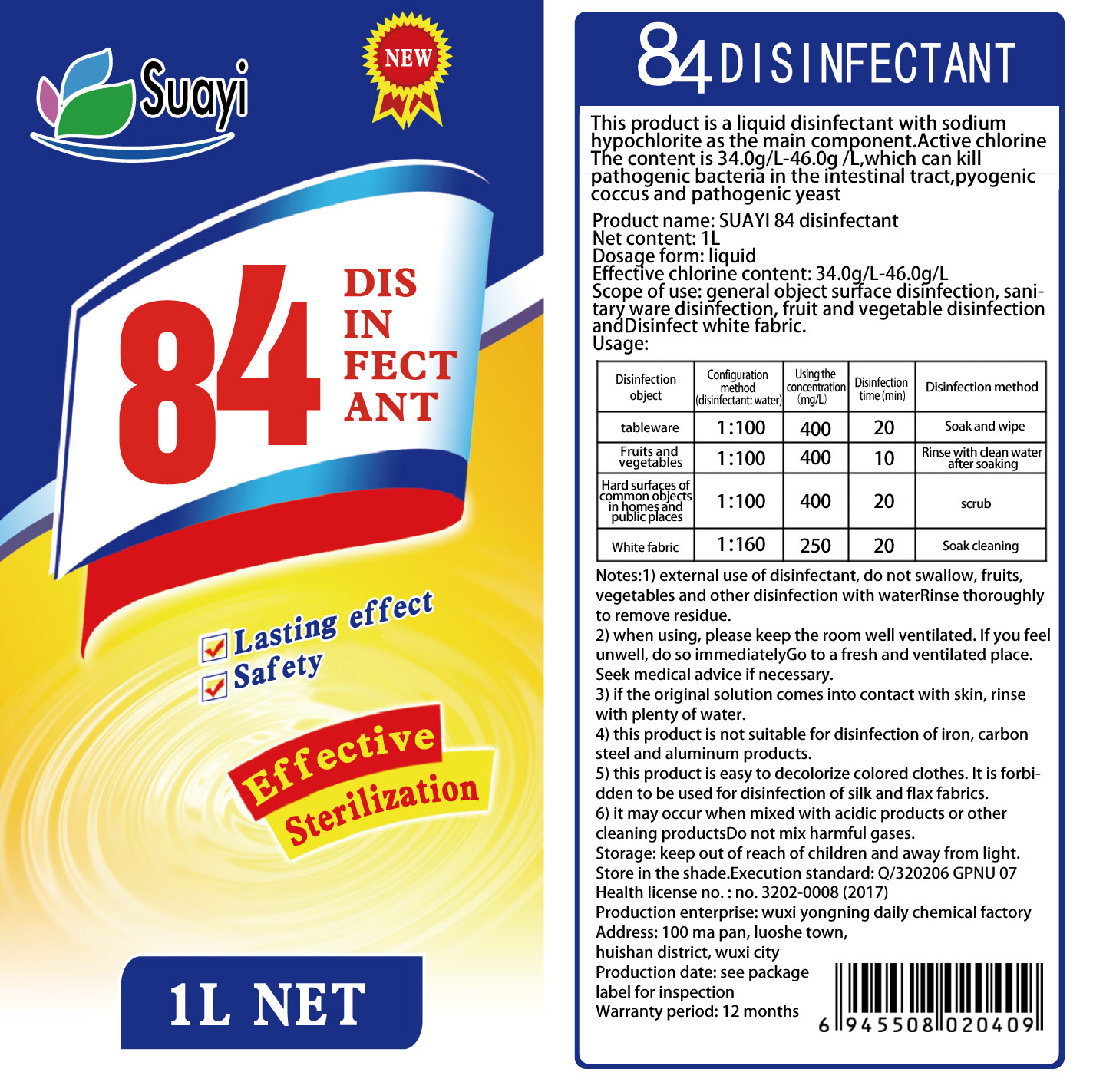 DRUG LABEL: 84 Disinfectant
NDC: 54607-001 | Form: LIQUID
Manufacturer: Wuxi Yongning Daily Chemical Factory
Category: otc | Type: HUMAN OTC DRUG LABEL
Date: 20200329

ACTIVE INGREDIENTS: SODIUM HYPOCHLORITE 40 g/1 L
INACTIVE INGREDIENTS: EDETIC ACID; SODIUM HYDROXIDE; SODIUM CHLORIDE; SODIUM ALLYLSULFONATE; WATER

INACTIVE INGREDIENT

water, sodium allylsulfonate, sodium chloride，EDTA，sodium hydroxide

PURPOSE

Disinfection
Sterilization
No Rinseing

WARNINGS

This product is not suitable for disinfection of iron, carbon steel and aluminum products.
This product is easy to decolorize colored clothes. It is forbidden to be used for disinfection of silk and flax fabrics.

It may occur when mixed with acidic products or other cleaning products.

Do not mix harmful gases.

keep out of reach of children.

INDICATIONS AND USAGE

External use of disinfectant, do not swallow, fruits,vegetables and other disinfection with waterRinse thoroughly to remove residue.

When using, please keep the room well ventilated. If you feel unwell, do so immediatelyGo to a fresh and ventilated place.
Seek medical advice if necessary.
If the original solution comes into contact with skin, rinse with plenty of water.

ACTIVE INGREDIENT

sodium hypochlorite

DOSAGE AND ADMINISTRATION

keep away from light.

Store in the shade.